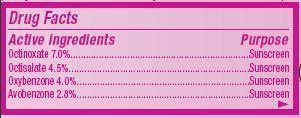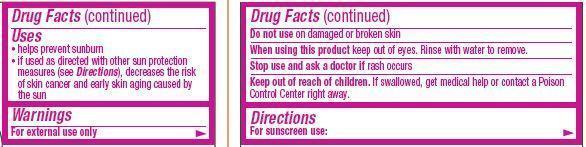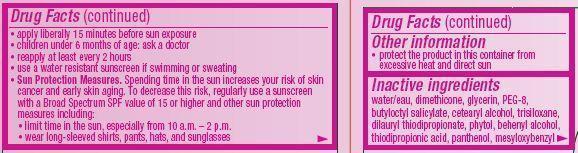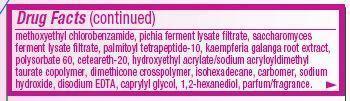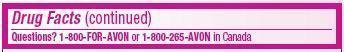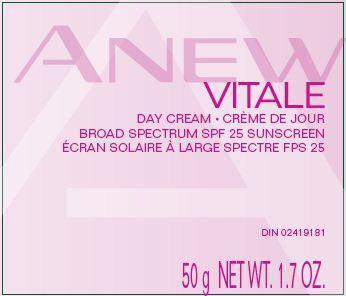 DRUG LABEL: Anew Vitale
NDC: 10096-0319 | Form: CREAM
Manufacturer: New Avon LLC
Category: otc | Type: HUMAN OTC DRUG LABEL
Date: 20190101

ACTIVE INGREDIENTS: OCTINOXATE 70 mg/1 g; OCTISALATE 45 mg/1 g; OXYBENZONE 40 mg/1 g; AVOBENZONE 28 mg/1 g
INACTIVE INGREDIENTS: WATER

Anew Vitale Day Cream Broad Spectrum SPF 25

Active Ingredients
Octinoxate 7.0%.................................
Octisalate 4.5%....................................
Oxybenzone 4.0%...............................
Avobenzone 2.8%..................................

Purpose
............... Sunscreen
............... Sunscreen
.............. Sunscreen

.............. Sunscreen

Uses

- helps prevent sunburn
- if used as directed with other sun protection measures (see Directions), decreases the risk of skin cancer and early skin aging caused by
  the sun

Warnings
For external use only

Do not use on damaged or broken skin

When using this product keep out of eyes. Rinse with water to remove.

Stop use and ask a doctor if rash occurs

Keep out of reach of children. If swallowed, get medical help or contact a Poison Control Center right away.

Directions

For sunscreen use:

- apply liberally 15 minutes before sun exposure
- children under 6 month of age:ask a doctor
- reapply at least every 2 hours
- use a water resistant sunscreen if swimming or sweating
- Sun Protection Measures. Spending time in the sun increases your risk of skin cancer and early skin aging. To decrease this risk, regularly use a sunscreen with a Broad Spectrum SPF value of 15 or higher and other sun protection measures including:
  • limit time in the sun, especially from 10 a.m. – 2 p.m.
  • wear long-sleeved shirts, pants, hats, and sunglasses

Other Information

- protect the product in this container from excessive heat and direct sun.

Inactive ingredients:
water/eau, dimethicone, glycerin, PEG-8, butyloctyl salicylate, cetearyl alcohol, trisiloxane, dilauryl thiodipropionate, phytol, behenyl alcohol,
thiodipropionic acid, panthenol, mesyloxybenzyl methoxyethyl chlorobenzamide, pichia ferment lysate filtrate, saccharomyces ferment lysate filtrate, palmitoyl tetrapeptide-10, kaempferia galanga root extract, polysorbate 60, ceteareth-20, hydroxyethyl acrylate/sodium acryloyldimethyl taurate copolymer, dimethicone crosspolymer, isohexadecane, carbomer, sodium hydroxide, disodium EDTA, caprylyl glycol, 1,2-hexanediol, parfum/fragrance.

Questions?
1-800-FOR-AVON or 1-800-265-AVON in Canada